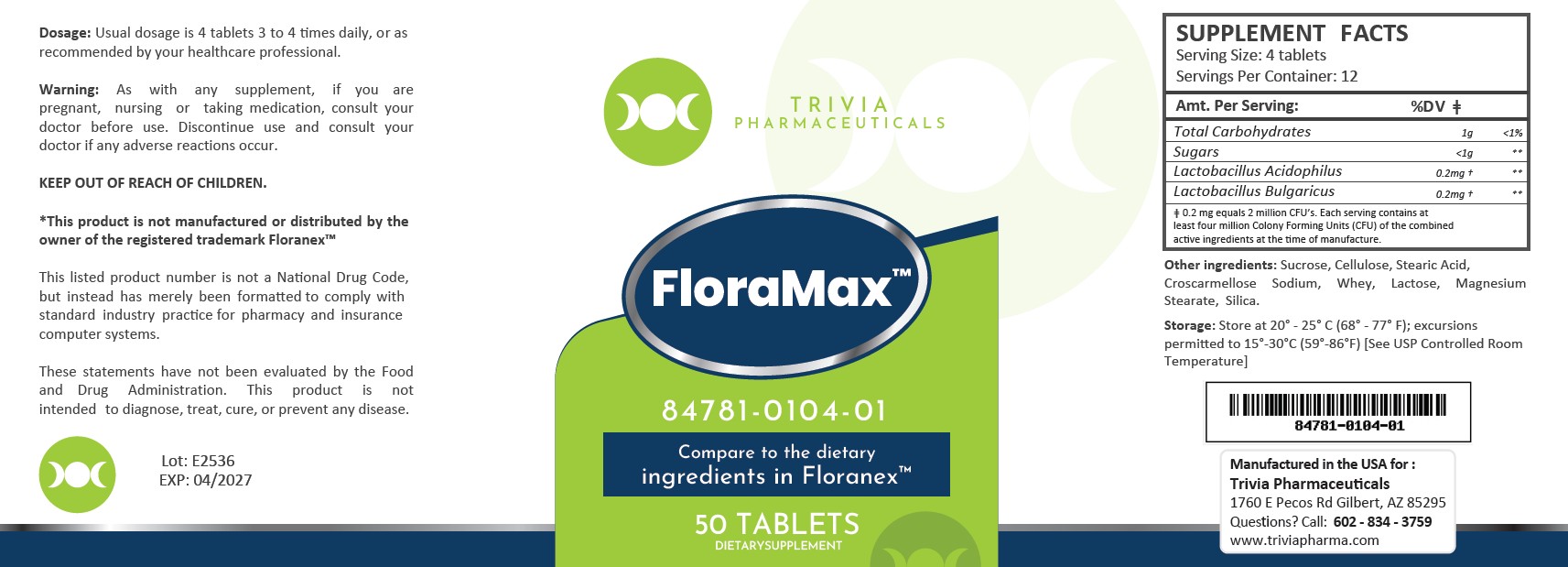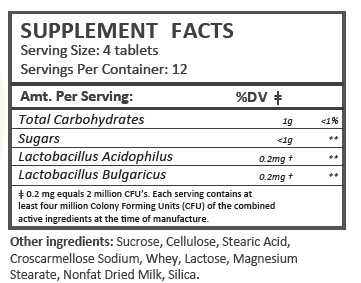 DRUG LABEL: FloraMax
NDC: 84781-104 | Form: TABLET
Manufacturer: Trivia Pharmaceuticals, LLC
Category: other | Type: DIETARY SUPPLEMENT
Date: 20250709

ACTIVE INGREDIENTS: LACTOBACILLUS ACIDOPHILUS 0.2 mg/1 1; LACTOBACILLUS DELBRUECKII BULGARICUS 0.2 mg/1 1
INACTIVE INGREDIENTS: SUCROSE; CELLULOSE, MICROCRYSTALLINE; CROSCARMELLOSE SODIUM; WHEY; MAGNESIUM STEARATE; STEARIC ACID; LACTOSE; SILICA

FloraMax Tablets

Supplement Facts

FloraMax Probiotic Tabs:

Description:

FloraMax is an orally administered probiotic formulation for the clinical dietary management of suboptimal nutritional status in patients where advanced supplementation is required and nutritional supplementation in physiologically stressful conditions for maintenance of good health is needed.

This listed product is not a National Drug Code, but instead has merely been formatted to comply with standard industry practice for pharmacy and insurance computer systems.

Warnings:

This product is contraindicated in patients with a known hypersensitivity to any of the ingredients, including milk products.

FloraMax should only be used under the direction and supervision of a licensed medical practitioner. Use with caution in patients that may have a medical condition, are pregnant, lactating, trying to conceive, under the age of 18, or taking medications.

Dosage:

Usual dosage is 4 tablets 3 to 4 times daily, or as recommended by your healthcare professional.

Packaging:

FloraMax is supplied as white, round tablets dispensed in plastic bottles of 50 ct.

84781-104-01

Reserved for Professional Recommendation

These statements have not been evaluated by the Food and Drug Administration. This product is not intended to diagnose, treat, cure, or prevent any disease.

Manufactured for:
Trivia Pharmaceuticals

Gilbert, AZ

Storage:

Store at 20° - 25° C (68° - 77° F); excursions permitted to 15°-30°C (59°-86°F) [See USP Controlled Room Temperature]